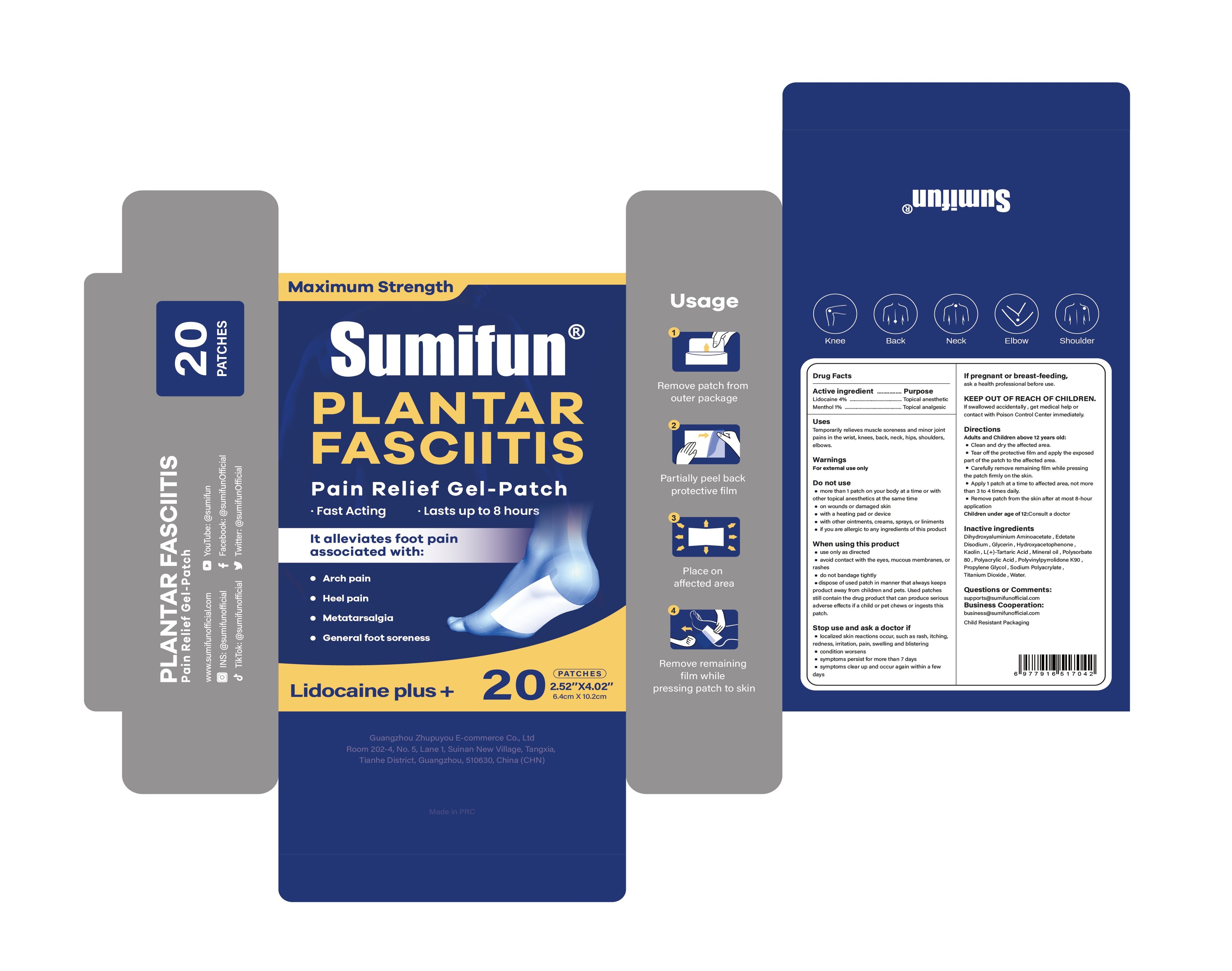 DRUG LABEL: Plantar Fasciitis Pain Relief Gel-Patch
NDC: 84165-007 | Form: PATCH
Manufacturer: Guangzhou Zhupuyou E-commerce Co., Ltd
Category: otc | Type: HUMAN OTC DRUG LABEL
Date: 20250506

ACTIVE INGREDIENTS: MENTHOL 1 g/100 g; LIDOCAINE 4 g/100 g
INACTIVE INGREDIENTS: GLYCERIN; DIHYDROXYALUMINUM AMINOACETATE ANHYDROUS; TITANIUM DIOXIDE; POLYACRYLIC ACID (250000 MW); POLYSORBATE 80; PROPYLENE GLYCOL; KAOLIN; HYDROXYACETOPHENONE; MINERAL OIL; POVIDONE K90; WATER; EDETATE DISODIUM; SODIUM POLYACRYLATE (2500000 MW); TARTARIC ACID

84165-007 Plantar Fasciitis Pain Relief Gel-Patch

ACTIVE INGREDIENT

LIDOCAINE 4%
MENTHOL 1%

PURPOSE

Topical anesthetic

INDICATIONS AND USAGE

Temporarily relieves muscle soreness and minor jointpains in the wrist, knees, back, neck, hips, shoulders,elbows.

WARNINGS

For external use only

DO NOT USE

more than 1 patch on your body at a time or withother topical anesthetics at the same time
on wounds or damaged skin
with a heating pad or device
with other ointments, creams, sprays, or liniments
if you are allergic to any ingredients of this product

WHEN USING

use only as directed
avoid contact with the eyes, mucous membranes, or rashes
do not bandage tightly
dispose of used patch in manner that always keepsproduct away from children and pets. Used patchesstill contain the drug product that can produce seriousadverse effects if a child or pet chews or ingests this patch.

STOP USE

localized skin reactions occur, such as rash, itching,redness, irritation, pain, swelling and blistering
econdition worsens
symptoms persist for more than 7 days
symptoms clear up and occur again within a few days

KEEP OUT OF REACH OF CHILDREN

lf swallowed accidentally , get medical help orcontact with Poison Control Center immediately.

DOSAGE AND ADMINISTRATION

Adults and Children above 12 years old:
Clean and dry the affected area.
Tear off the protective film and apply the exposedpart of the patch to the affected area.
Carefully remove remaining film while pressingthe patch fimmly on the skin.
Apply 1 patch at a time to affected area, not morethan 3 to 4 times daily.
Remove patch from the skin after at most 8-hourapplication
Children under age of 12:Consult a doctor

INACTIVE INGREDIENT

Dihydroxyaluminum Aminoacetate
Edetate Disodium
Glycerin
Hydroxyacetophenone
Kaolin
Mineral Oil
Polyacrylic Acid
Polysorbate 80
PolyvinylPyrrolidone
Propylene Glycol
Sodium Polyacrylate
Tartaric Acid
Titanium Dioxide
Water